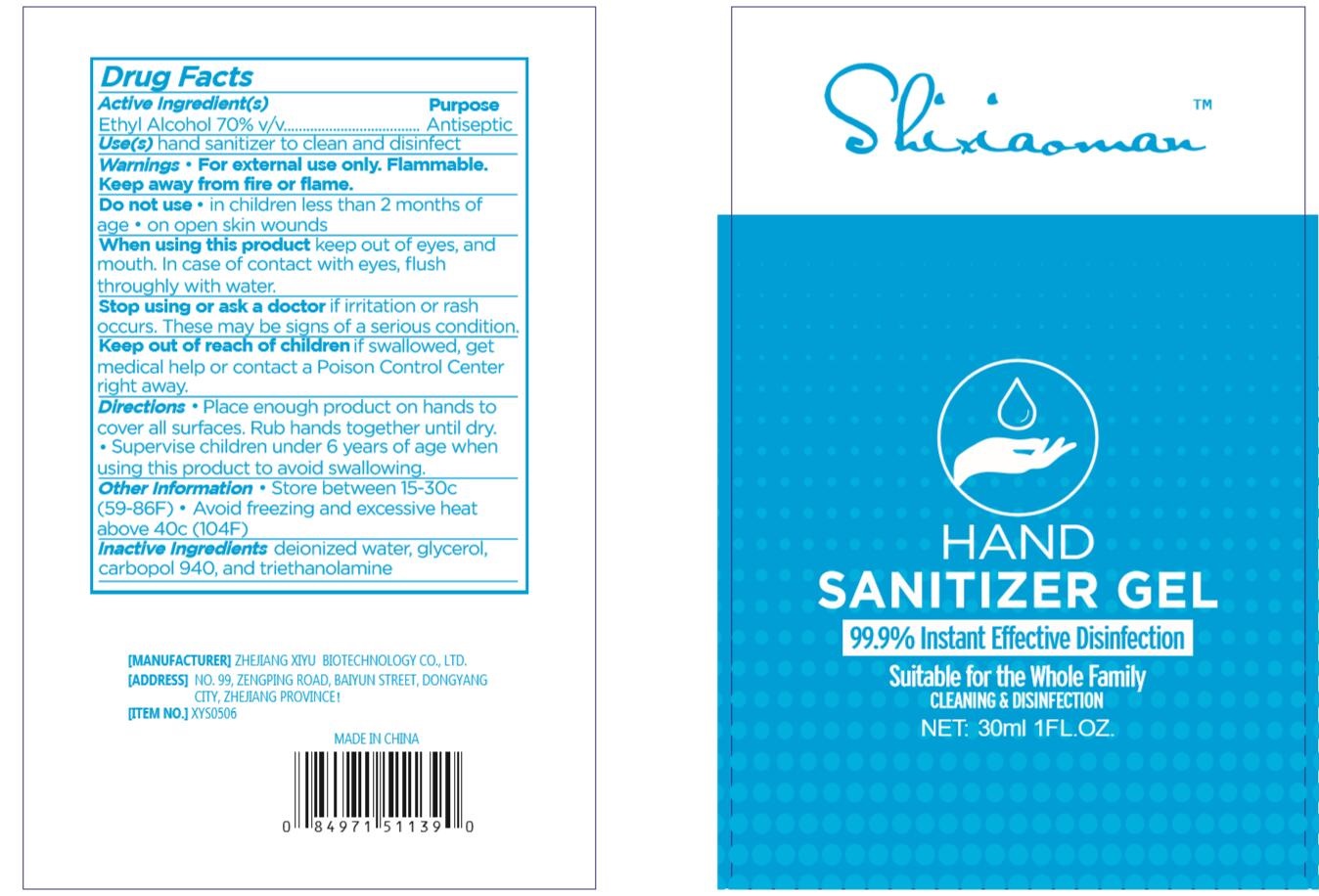 DRUG LABEL: Shixiaoman HAND SANITIZER
NDC: 77360-002 | Form: GEL
Manufacturer: Zhejiang XiYu Biotechnology Co., Ltd.
Category: otc | Type: HUMAN OTC DRUG LABEL
Date: 20200514

ACTIVE INGREDIENTS: ALCOHOL 70 mL/100 mL
INACTIVE INGREDIENTS: WATER; CARBOMER 940; TROLAMINE; GLYCERIN

HAND SANITIZER

Active ingredient

Ethyl Alcohol 70% v/v

Purpose

Antiseptic

Use

hand sanitizer to clean and disinfect

Warnings

For external use only.

Flammable.Keep product away from fire or flame.

Do not use in children less than 2 months of age. On open skin wounds.

When using this product

keep out of eyes, and mouth. In case of contact with eye, flush throughly with water

Stop use and ask a doctor if

irritation or rash occurs. These may be signs of serious condition.

Keep out of reach of children.

If swallowed, get medical help or contact a Poison Control Center right away.

Directions

Place enough product on your hands to cover all surfaces. Rub hands together until dry.

Spervise children under 6 years of age when using this product to avoid swallowing.

Inactive ingredients

deionized water, glycerol, carbopol 940, and triethanolamine

Other information:

Store below 15-30 ℃ (59-86℉).

Avoid freezing and excessive heat above 40 ℃ (104℉)